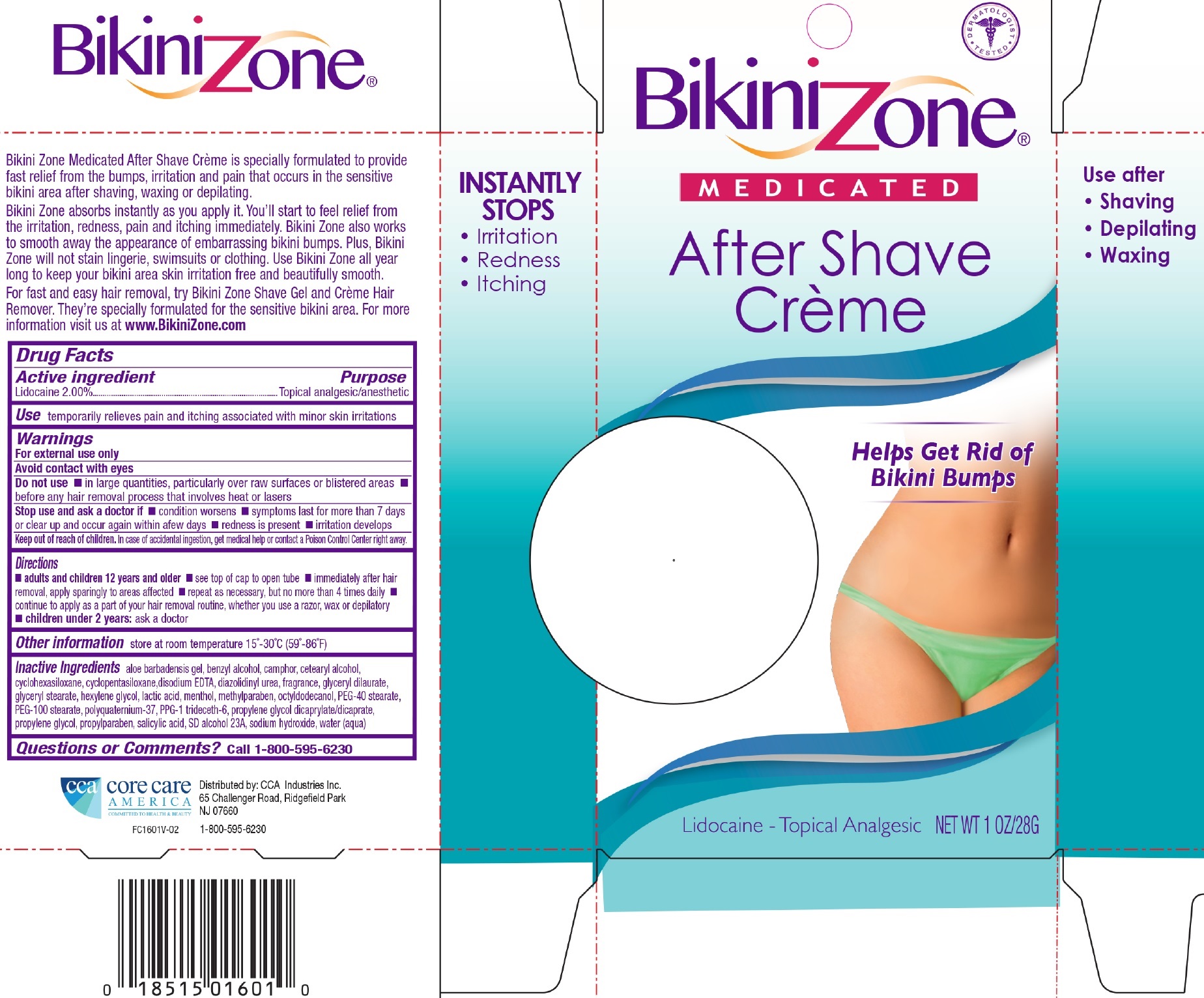 DRUG LABEL: Bikini Zone Medicated CREME
NDC: 61543-1601 | Form: CREAM
Manufacturer: CCA Industries, Inc.
Category: otc | Type: HUMAN OTC DRUG LABEL
Date: 20221216

ACTIVE INGREDIENTS: LIDOCAINE 2 g/100 g
INACTIVE INGREDIENTS: BENZYL ALCOHOL; CAMPHOR (NATURAL); CETOSTEARYL ALCOHOL; CYCLOMETHICONE 6; CYCLOMETHICONE 5; EDETATE DISODIUM; DIAZOLIDINYL UREA; GLYCERYL MONOSTEARATE; HEXYLENE GLYCOL; LACTIC ACID; MENTHOL; METHYLPARABEN; OCTYLDODECANOL; POLYOXYL 100 STEARATE; PROPYLENE GLYCOL DICAPRYLATE; PROPYLENE GLYCOL; PROPYLPARABEN; SALICYLIC ACID; SODIUM HYDROXIDE; WATER

Bikini Zone Medicated CREME

Active Ingredient

LIDOCAINE 2.00%

Purpose

topical analgesic/anesthetic

Use

temporarily relieves pain and itching associated with minor skin irritation.

Warnings

For external use only.

Avoid contact with eyes

Do not use

- in large quantities, particularly over raw surfaces or blistered areas.
- before any hair removal process that involves heat or lasers

Stop use and ask a doctor if

- Condition worsens
- Symptoms last for more than 7 days or clear up and occur again within a few days.
- redness is present
- irritation develops

Keep out of reach of children

In case of accidental ingestion, get medical help or contact a Poison Control Center right away.

Directions

adults and children 12 years and older

- see top of cap to open tube
- immediately after hair removal, apply sparingly to areas affected
- repeat as necessary, but no more than 4 times daily
- continue to apply as a part of your hair removal routine, whether you use a razor, wax or depilatory.
- children under 2 years: ask a doctor

Other information

store at room temperature 15°-30°C (59°-86°F)

Inactive Ingredients

aloe barbadensis gel, benzyl alcohol, camphor, cetearyl alcohol, cyclohexasiloxane, cyclopentasiloxane, disodium edta, diazolidinyl urea, fragrance, glyceryl dilaurate, glyceryl stearate, hexylene glycol, lactic acid, menthol, methylparaben, octyldodecanol, peg-40 stearate, peg-100 stearate, polyquaternium-37, ppg-1 trideceth-6, propylene glycol dicaprylate/dicaprate, propylene glycol, propylparaben, salicylic acid, sd alcohol 23a, sodium hydroxide, water (aqua).

Questions or Comments?

Call 1-800-595-6230